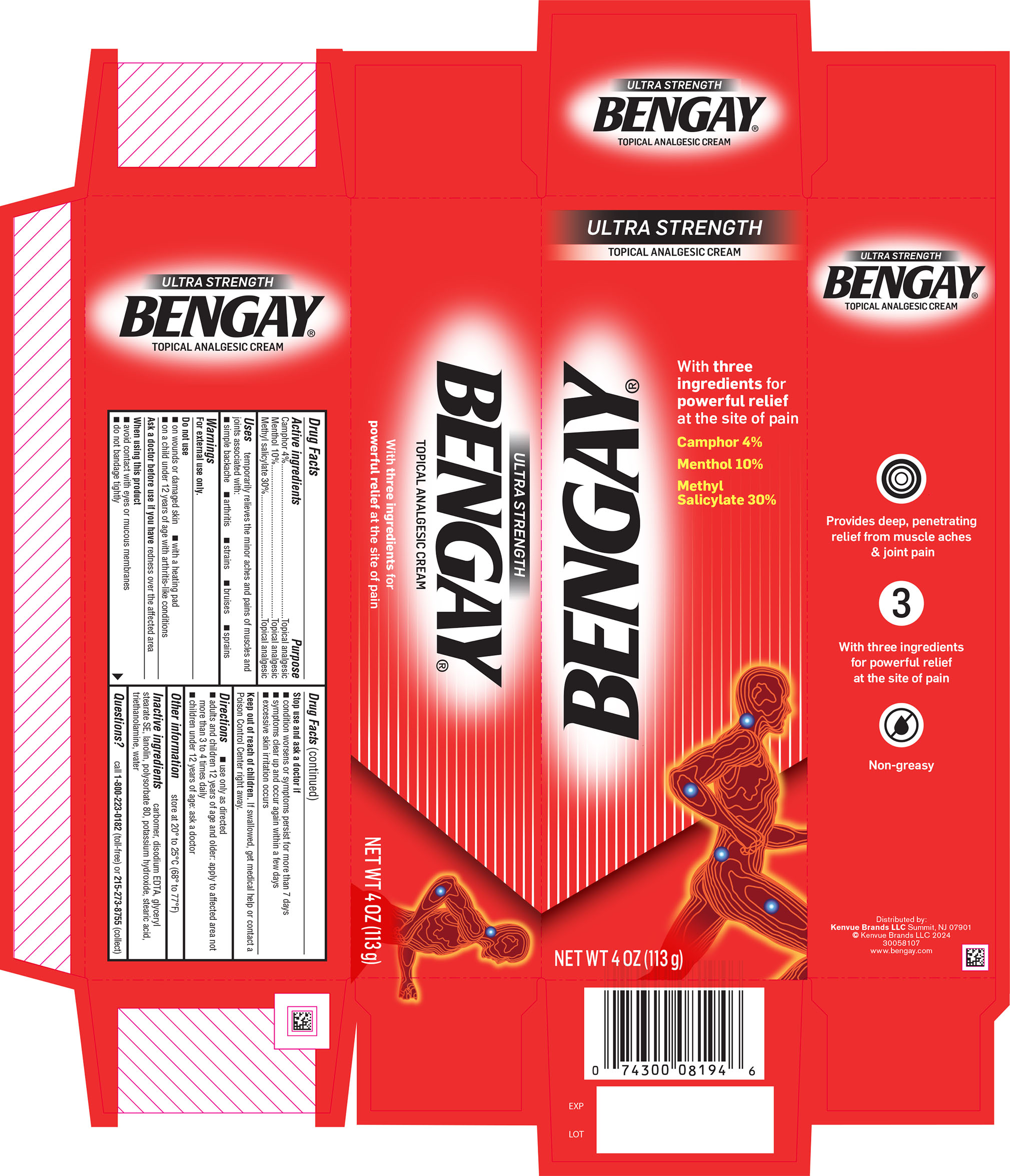 DRUG LABEL: BENGAY ULTRA STRENGTH NON-GREASY
NDC: 69968-0538 | Form: CREAM
Manufacturer: Kenvue Brands LLC
Category: otc | Type: HUMAN OTC DRUG LABEL
Date: 20241211

ACTIVE INGREDIENTS: CAMPHOR (SYNTHETIC) 40 mg/1 g; MENTHOL, UNSPECIFIED FORM 100 mg/1 g; METHYL SALICYLATE 300 mg/1 g
INACTIVE INGREDIENTS: CARBOMER HOMOPOLYMER, UNSPECIFIED TYPE; EDETATE DISODIUM ANHYDROUS; GLYCERYL STEARATE SE; LANOLIN; POLYSORBATE 80; POTASSIUM HYDROXIDE; STEARIC ACID; TROLAMINE; WATER

BENGAY® ULTRA STRENGTH NON-GREASY CREAM

Drug Facts

ACTIVE INGREDIENT

Active ingredient | Purpose
Camphor 4% | Topical analgesic
Menthol 10% | Topical analgesic
Methyl salicylate 30% | Topical analgesic

Use

temporarily relieves the minor aches and pains of muscles and joints associated with:

- simple backache
- arthritis
- strains
- bruises
- sprains

Warnings

For external use only.

Do not use

- on wounds or damaged skin
- with a heating pad
- on a child under 12 years of age with arthritis-like conditions

Ask a doctor before use if you have redness over affected area

When using this product

- avoid contact with eyes or mucous membranes
- do not bandage tightly

Stop use and ask a doctor if

- condition worsens or symptoms persist for more than 7 days
- symptoms clear up and occur again within a few days
- excessive skin irritation occurs

Keep out of reach of children. If swallowed, get medical help or contact a Poison Control Center right away.

Directions

- use only as directed
- adults and children 12 years of age and older: apply to affected area not more than 3 to 4 times daily
- children under 12 years of age: ask a doctor

Other information

store at 20° to 25°C (68° to 77°F)

Inactive ingredients

carbomer, disodium EDTA, glyceryl stearate SE, lanolin, polysorbate 80, potassium hydroxide, stearic acid, triethanolamine, water

Questions?

call 1-800-223-0182 (toll-free) or 215-273-8755 (collect)

Distributed by:
Kenvue Brands LLC
Summit, NJ 07901

PRINCIPAL DISPLAY PANEL - 113 g Tube Carton

ULTRA STRENGTH
TOPICAL ANALGESIC CREAM

BENGAY®

With three
ingredients for
powerful relief
at the site of pain

Camphor 4%
Menthol 10%
Methyl
Salicylate 30%

NET WT 4 OZ (113 g)